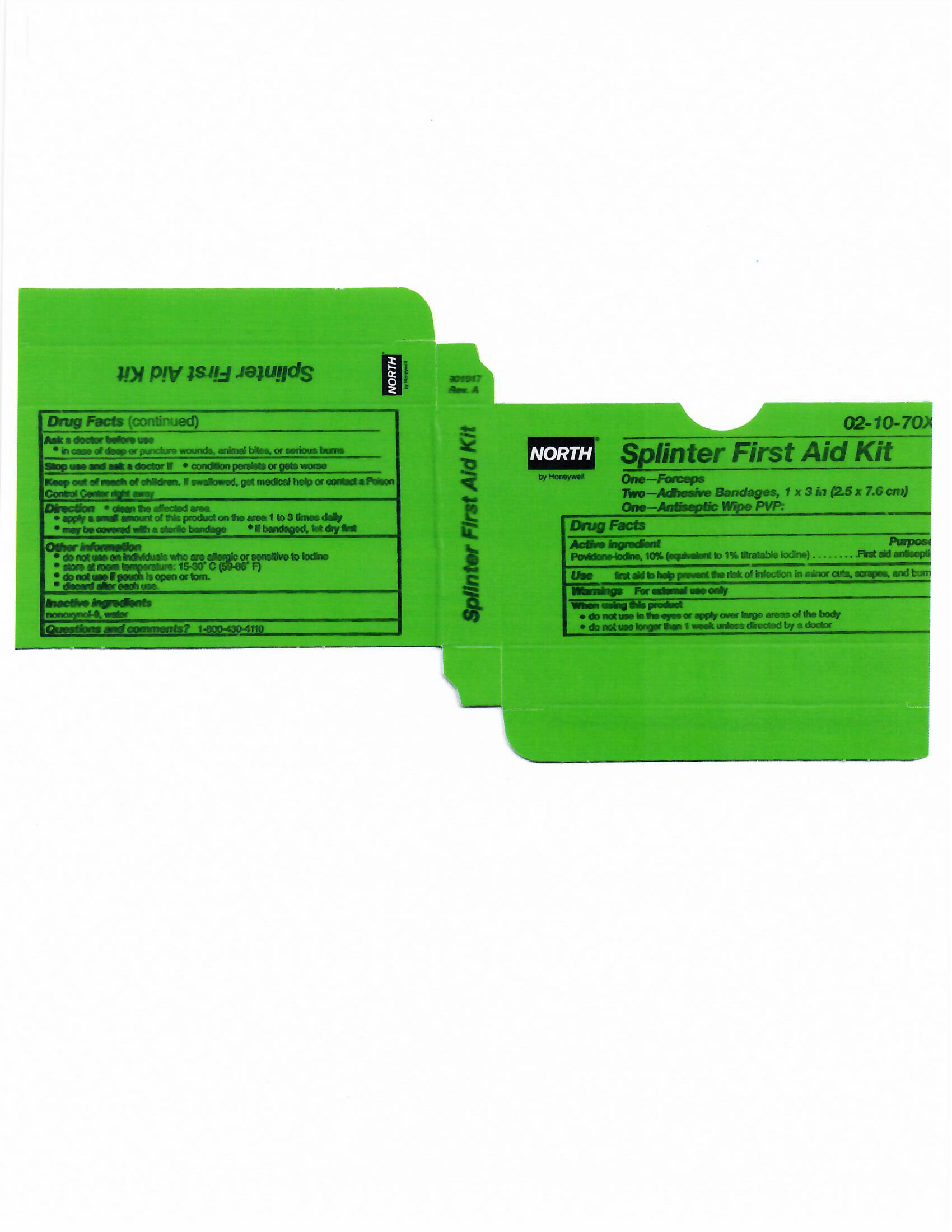 DRUG LABEL: Splinter First Aid Kit
NDC: 0498-9002 | Form: KIT | Route: TOPICAL
Manufacturer: Honeywell  Safety Products USA, Inc
Category: otc | Type: HUMAN OTC DRUG LABEL
Date: 20180823

ACTIVE INGREDIENTS: POVIDONE-IODINE 10 mg/1 mL
INACTIVE INGREDIENTS: NONOXYNOL-9; WATER

Splint First Aid Kit: 02-10-70X

Active ingredient

Povidone iodine 10% (equivalent to 1% titrateable iodine)

Purpose

First aid antiseptic

Uses

- first aid antiseptic to help prevent infection in minor cuts, scrapes and burns

Warnings

For external use only

Ask a doctor before use if you have

- deep or puncture wounds
- animal bites
- serious burns

Stop use and ask a doctor if

- condition worsens or persists for more than 72 hours
- irritation and redness develops

Keep out of reach of children.

If swallowed, get medical help or contact a Poison Control Center right away

Directions

- clean the affected area
- apply1 to 3 times daily
- may be covered with a sterile bandage
- if bandaged, let dry first

Other information

- do not use on individuals who are allergic or sensitive to iodine
- store at controlled temperature 59-86ºF (15-30ºC)
- do not use if pouch is open or torn
- discard after each use

Inactive ingredients

nonoxynol 9, water

Questions

1-800-430-5490